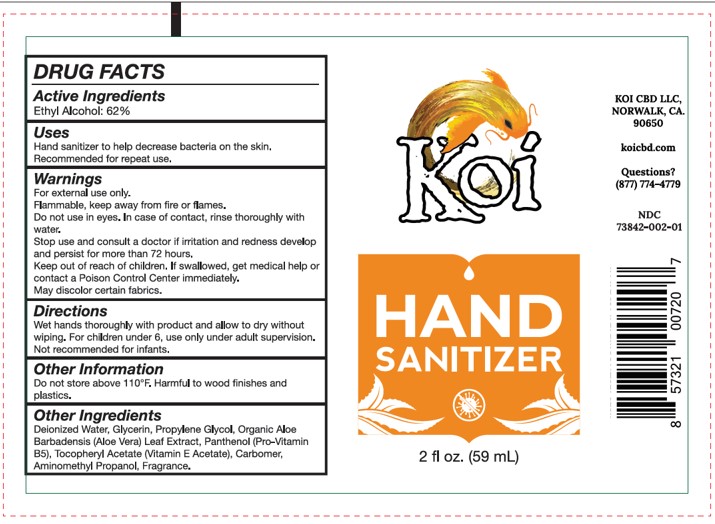 DRUG LABEL: Koi Hand Sanitizer
NDC: 73842-002 | Form: GEL
Manufacturer: Koi CBD LLC
Category: otc | Type: HUMAN OTC DRUG LABEL
Date: 20200414

ACTIVE INGREDIENTS: ALCOHOL 62 g/100 mL
INACTIVE INGREDIENTS: CARBOMER HOMOPOLYMER, UNSPECIFIED TYPE; PROPYLENE GLYCOL; ALPHA-TOCOPHEROL ACETATE; AMINOMETHYLPROPANOL; WATER; GLYCERIN; ALOE VERA LEAF; PANTHENOL

Koi Hand Sanitizer

ACTIVE INGREDIENT

Ethyl Alcohol 62%...... Antimicrobial

PURPOSE

Antimicrobial

INDICATIONS AND USAGE

Hand sanitizer to help decrease bacteria on the skin. Recommended for repeat use.

WARNINGS

For external use only. Flammable, keep away from fire or flames.

Do not use in eyes. In case of contact, rinse thoroughly with water.

Stop use and consult a doctor if irritation and redness develop and persist for more than 72 hours.

Keep out of reach of children. If swallowed, get medical help or contact a Poison Control Center immediately.

DOSAGE AND ADMINISTRATION

Wet hands thoroughly with product and allow to dry without wiping. For children under 6, use only under adult supervision. Not recommended for infants.

STORAGE AND HANDLING

Do not store about 110°F. Harmful to wood finishes and plastics.

INACTIVE INGREDIENT

Deionized Water, Glycerin, Propylene Glycol, Organic Aloe Barbadensis (Aloe Vera) Leaf Extract, Panthenol (Pro-Vitamin B5), Tocopheryl Acetate (Vitamin E Acetate), Carbomer, Aminomethyl Propanol, Fragrance.

PACKAGE LABEL

59 mL NDC: 73842-002-01